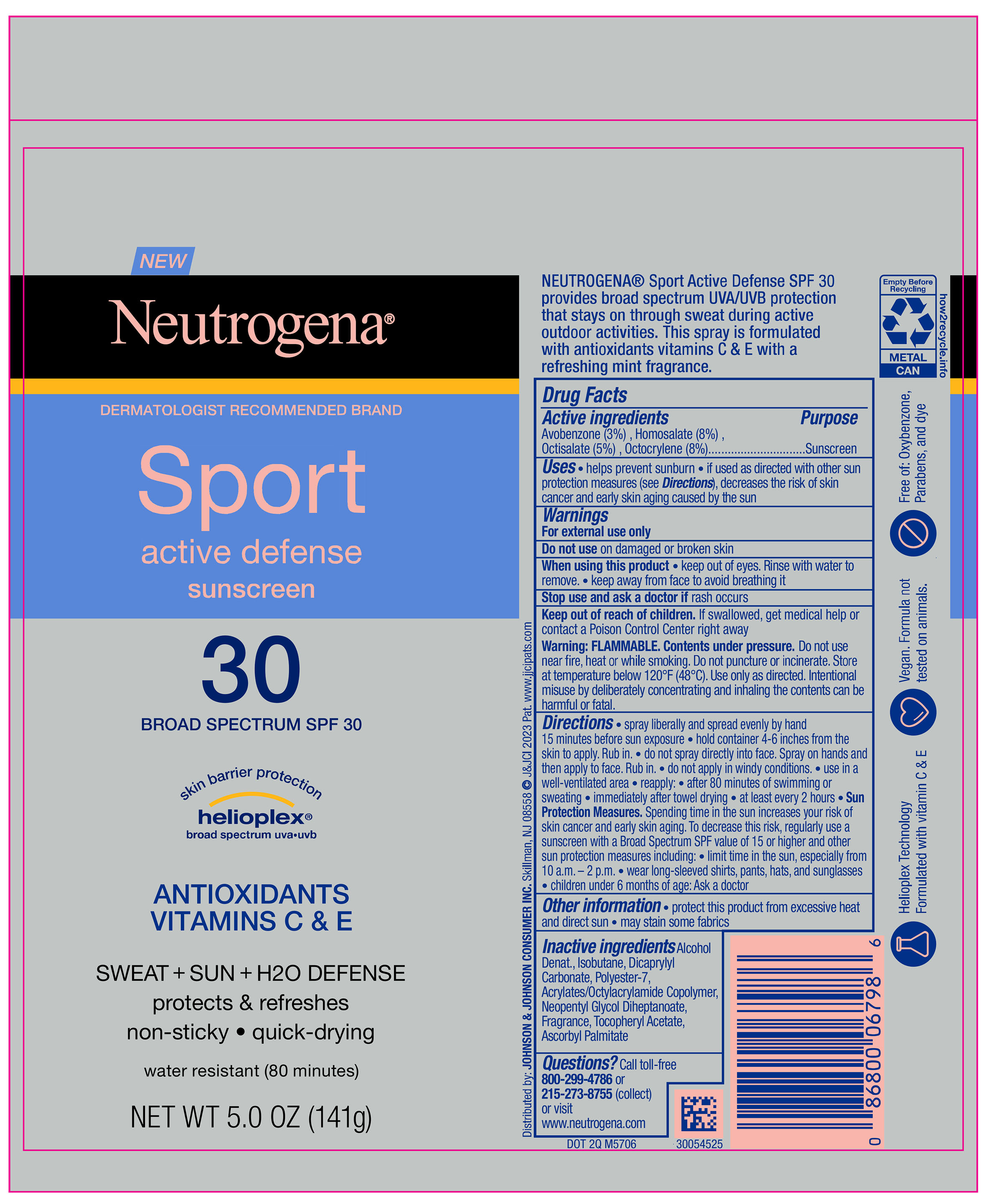 DRUG LABEL: Neutrogena Sport Active Defense SPF 30
NDC: 69968-0824 | Form: SPRAY
Manufacturer: Kenvue Brands LLC
Category: otc | Type: HUMAN OTC DRUG LABEL
Date: 20251008

ACTIVE INGREDIENTS: AVOBENZONE 30 mg/1 g; HOMOSALATE 80 mg/1 g; OCTOCRYLENE 80 mg/1 g; OCTISALATE 50 mg/1 g
INACTIVE INGREDIENTS: ALCOHOL; DICAPRYLYL CARBONATE; POLYESTER-7; NEOPENTYL GLYCOL DIHEPTANOATE; ACRYLATE/ISOBUTYL METHACRYLATE/N-TERT-OCTYLACRYLAMIDE COPOLYMER (75000 MW); ISOBUTANE; ALPHA-TOCOPHEROL ACETATE; ASCORBYL PALMITATE

Neutrogena Sport Active Defense SPF 30

Drug Facts

ACTIVE INGREDIENT

Active ingredients | Purpose
Avobenzone (3%), | Sunscreen
Homosalate (8%), | Sunscreen
Octisalate (5%), | Sunscreen
Octocrylene (8%) | Sunscreen

Uses

• helps prevent sunburn

• if used as directed with other sun protection measures (see Directions), decreases the risk of skin cancer and early skin aging caused by the sun

Warnings

For external use only

Do not use on damaged or broken skin

When using this product

• keep out of eyes. Rinse with water to remove.

• keep away from face to avoid breathing it

Stop use and ask a doctor if rash occurs

Keep out of reach of children. If swallowed, get medical help or contact a Poison Control Center right away

Warning: FLAMMABLE. Contents under pressure. Do not use near fire, heat or while smoking. Do not puncture or incinerate. Store at temperature below 120°F (48°C). Use only as directed. Intentional misuse by deliberately concentrating and inhaling the contents can be harmful or fatal.

Directions

• spray liberally and spread evenly by hand 15 minutes before sun exposure

• hold container 4-6 inches from the skin to apply. Rub in.

• do not spray directly into face. Spray on hands and then apply to face. Rub in.

• do not apply in windy conditions.

• use in a well-ventilated area

• reapply:

• after 80 minutes of swimming or sweating

• immediately after towel drying

• at least every 2 hours

• Sun Protection Measures: Spending time in the sun increases your risk of skin cancer and early skin aging. To decrease this risk, regularly use a sunscreen with a Broad Spectrum SPF value of 15 or higher and other sun protection measures including:

• limit time in the sun, especially from 10 a.m. – 2 p.m.

• wear long-sleeved shirts, pants, hats, and sunglasses

• children under 6 months of age: Ask a doctor

Other information

• protect this product from excessive heat and direct sun

• may stain some fabrics

Inactive ingredients

Alcohol Denat., Isobutane, Dicaprylyl Carbonate, Polyester-7, Acrylates/Octylacrylamide Copolymer, Neopentyl Glycol Diheptanoate, Fragrance, Tocopheryl Acetate, Ascorbyl Palmitate

Questions?

Call toll-free 800-299-4786 or 215-273-8755 (collect) or visit www. neutrogena.com

Distributed by:
JOHNSON & JOHNSON CONSUMER INC.
Skillman, NJ 08558

PRINCIPAL DISPLAY PANEL - 141 g Can Label

NEW

Neutrogena®

DERMATOLOGIST RECOMMENDED BRAND

Sport

active defense

sunscreen

30

BROAD SPECTRUM SPF 30

skin barrier protection

helioplex®

broad spectrum uva●uvb

ANTIOXIDANTS

VITAMINS C & E

SWEAT + SUN + H2O DEFENSE

protects & refreshes

non-sticky ● quick-drying

water resistant (80 minutes)

NET WT 5.0 OZ (141 g)